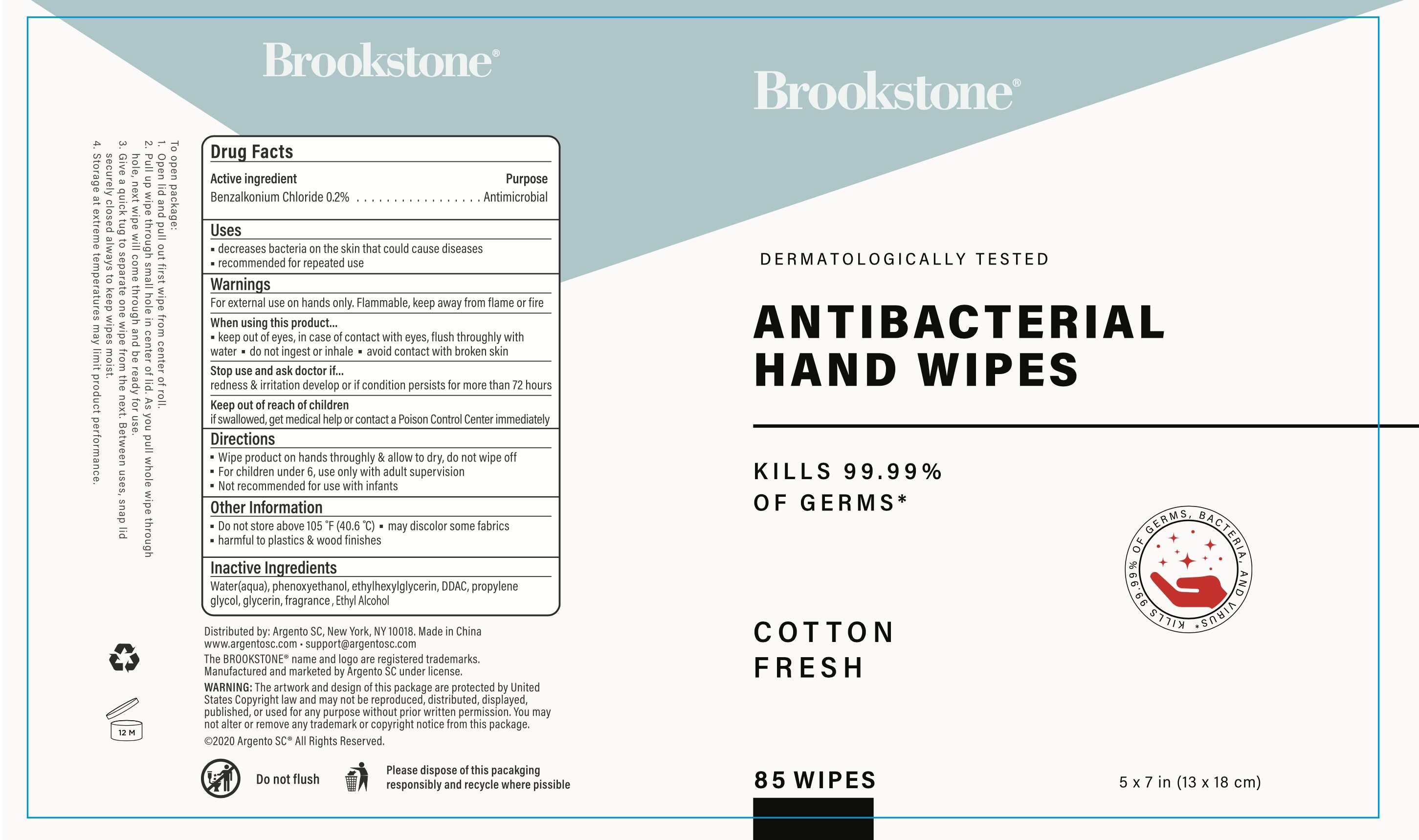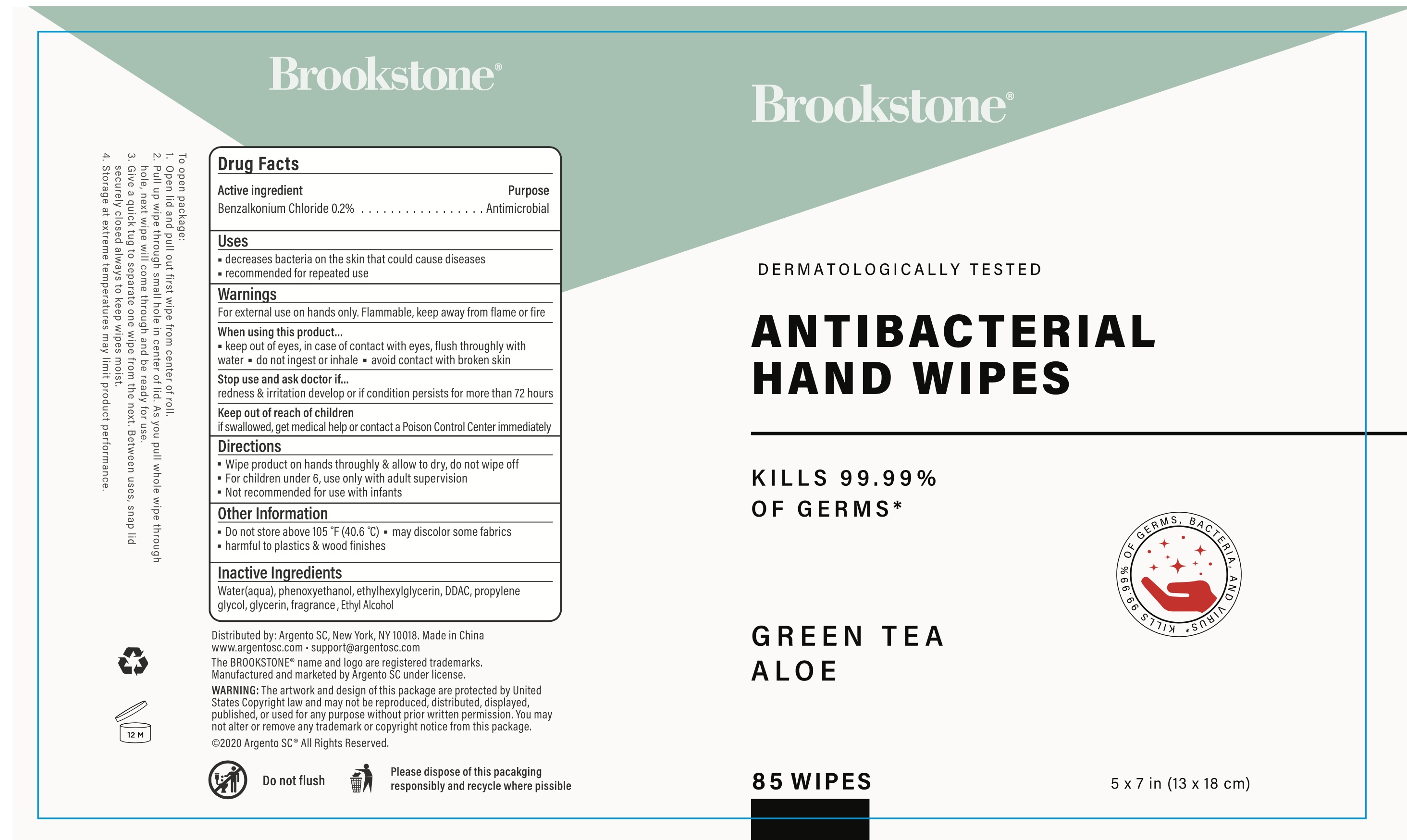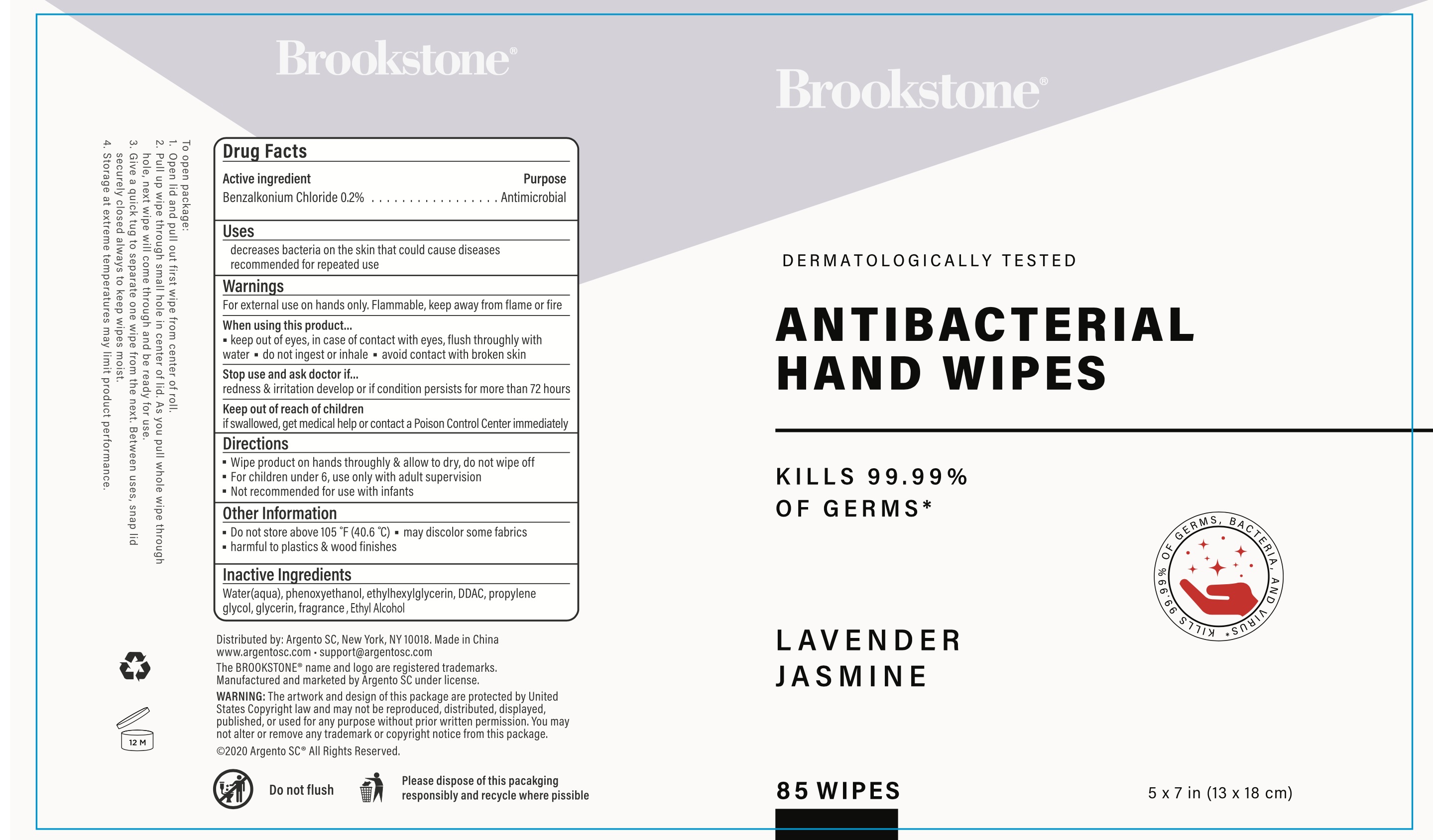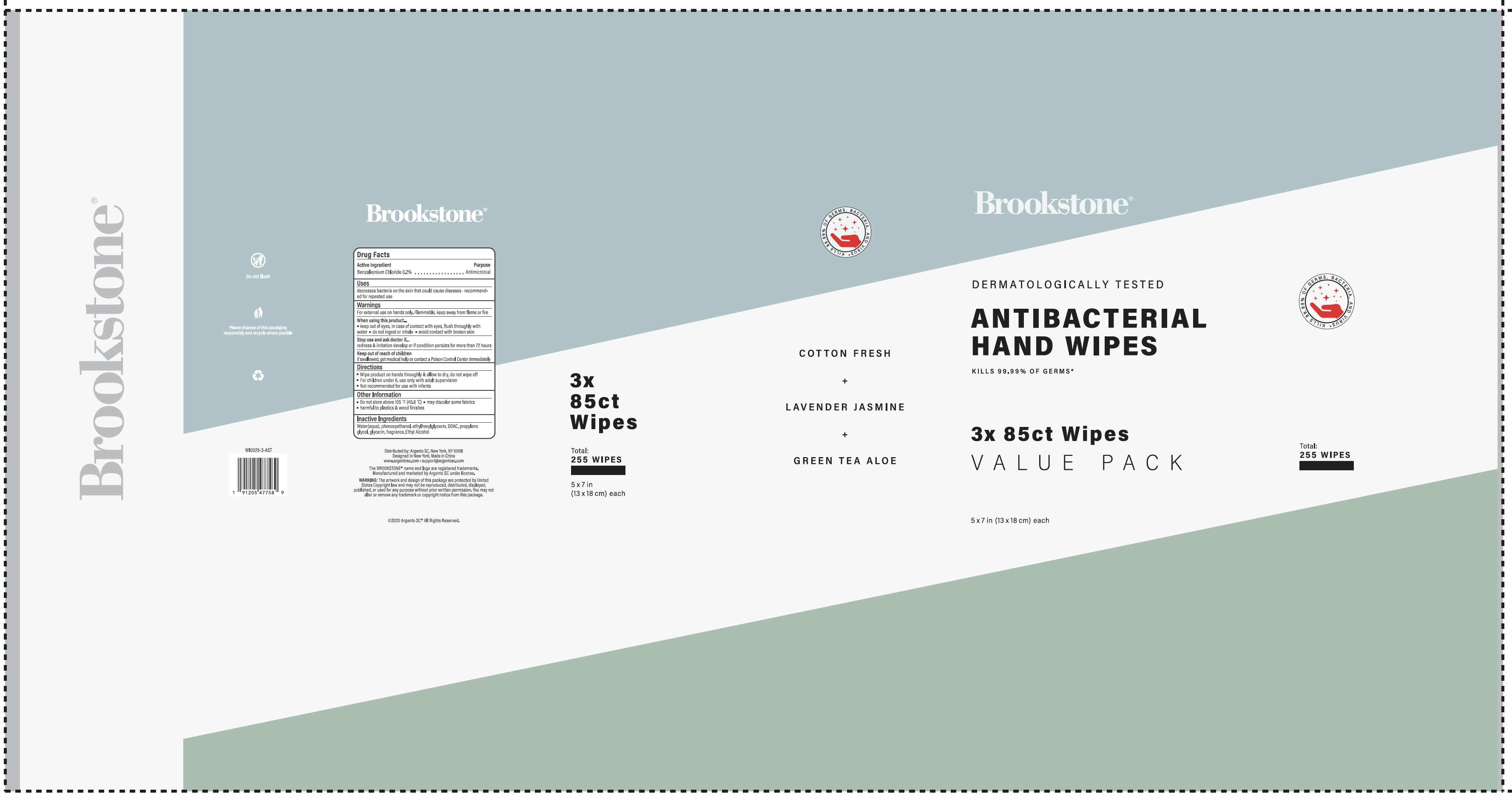 DRUG LABEL: BROOKSTONE ANTIBACTERIAL HAND WIPES Value Pack
NDC: 77731-009 | Form: KIT | Route: TOPICAL
Manufacturer: Argento sc by sicura inc.
Category: otc | Type: HUMAN OTC DRUG LABEL
Date: 20200618

ACTIVE INGREDIENTS: BENZALKONIUM CHLORIDE 6 mg/1 1; BENZALKONIUM CHLORIDE 6 mg/1 1; BENZALKONIUM CHLORIDE 6 mg/1 1
INACTIVE INGREDIENTS: WATER; GLYCERIN; ETHYLHEXYLGLYCERIN; PHENOXYETHANOL; PROPYLENE GLYCOL; ALCOHOL; WATER; GLYCERIN; ETHYLHEXYLGLYCERIN; PHENOXYETHANOL; PROPYLENE GLYCOL; ALCOHOL; WATER; GLYCERIN; ETHYLHEXYLGLYCERIN; PHENOXYETHANOL; PROPYLENE GLYCOL; ALCOHOL

BROOKSTONE ANTIBACTERIAL HAND WIPES Value Pack

BROOKSTONE ANTIBACTERIAL HAND WIPES Cotton Fresh

Active Ingredient

Benzalkonium Chloride 0.2%

Purpose

Antimicrobial

Use

Decrease bacteria on skin that could cause disease

Recommended for repeated use

WARNINGS

For external use only. Flammable, keep way from flame or fire

When using this product, keep out of eyes. In case of contact with eyes, flush thoroughly with water

Do not ingest or inhale

Avoid contact with broken skin

Stop Use

Stop use and ask a doctor if irrigation and redness develop or if condition persists for more than 72 hours

Keep out of reach of children, if swallowed, get medical help or contact a Poison Control Center immediately

Directions

- Wipe product on hands thoroughly and allow to dry, do not wipe off
- For children under 6, use under adult supervision
- Not recommended for use with infants

Other Information

Do not store above 105F (40.6C)

May discolor some fabrics

Harmful to plastics and wood finishes

Inactive ingredients

Water, Glycerin, Ethylhexylglycerin, DDAC, Phenoxyethanol, Propylene Glycol, Fragrance

BROOKSTONE ANTIBACTERIAL HAND WIPES Lavender Jasmine

Active Ingredient

Benzalkonium Chloride 0.2%

Purpose:

Antimicrobial

Uses:

Decrease bacteria on skin that could cause disease

Recommended for repeated use

Warnings

For external use only. Flammable, keep way from flame or fire

When using this product, keep out of eyes. In case of contact with eyes, flush thoroughly with water

Do not ingest or inhale

Avoid contact with broken skin

Stop Use

Stop use and ask a doctor if irrigation and redness develop or if condition persists for more than 72 hours

Keep out of reach of children, if swallowed,get medical help or contact a Poison Control Center immediately

Directions

- Wipe product on hands thoroughly and allow to dry, do not wipe off
- For children under 6, use under adult supervision
- Not recommended for use with infants

Other Information

Do not store above 105F (40.6C)

May discolor some fabrics

Harmful to plastics and wood finishes

Inactive Ingredients

Water, Glycerin, Ethylhexylglycerin, DDAC, Phenoxyethanol, Propylene Glycol, Fragrance

BROOKSTONE ANTIBACTERIAL HAND WIPES Green Tea Aloe

Active Ingredient

Benzalkonium Chloride 0.2%

Purpose

Antimicrobial

Uses

Decrease bacteria on skin that could cause disease

Recommended for repeated use

Warnings

For external use only. Flammable, keep way from flame or fire

When using this product, keep out of eyes. In case of contact with eyes, flush thoroughly with water

Do not ingest or inhale

Avoid contact with broken skin

Stop Use

Stop use and ask a doctor if irrigation and redness develop or if condition persists for more than 72 hours

Keep out of reach of children, if swallowed,get medical help or contact a Poison Control Center immediately

Directions

- Wipe product on hands thoroughly and allow to dry, do not wipe off
- For children under 6, use under adult supervision
- Not recommended for use with infants

Other Information

Do not store above 105F (40.6C)

May discolor some fabrics

Harmful to plastics and wood finishes

Inactive Ingredients

Water, Glycerin, Ethylhexylglycerin, DDAC, Phenoxyethanol, Propylene Glycol, Fragrance